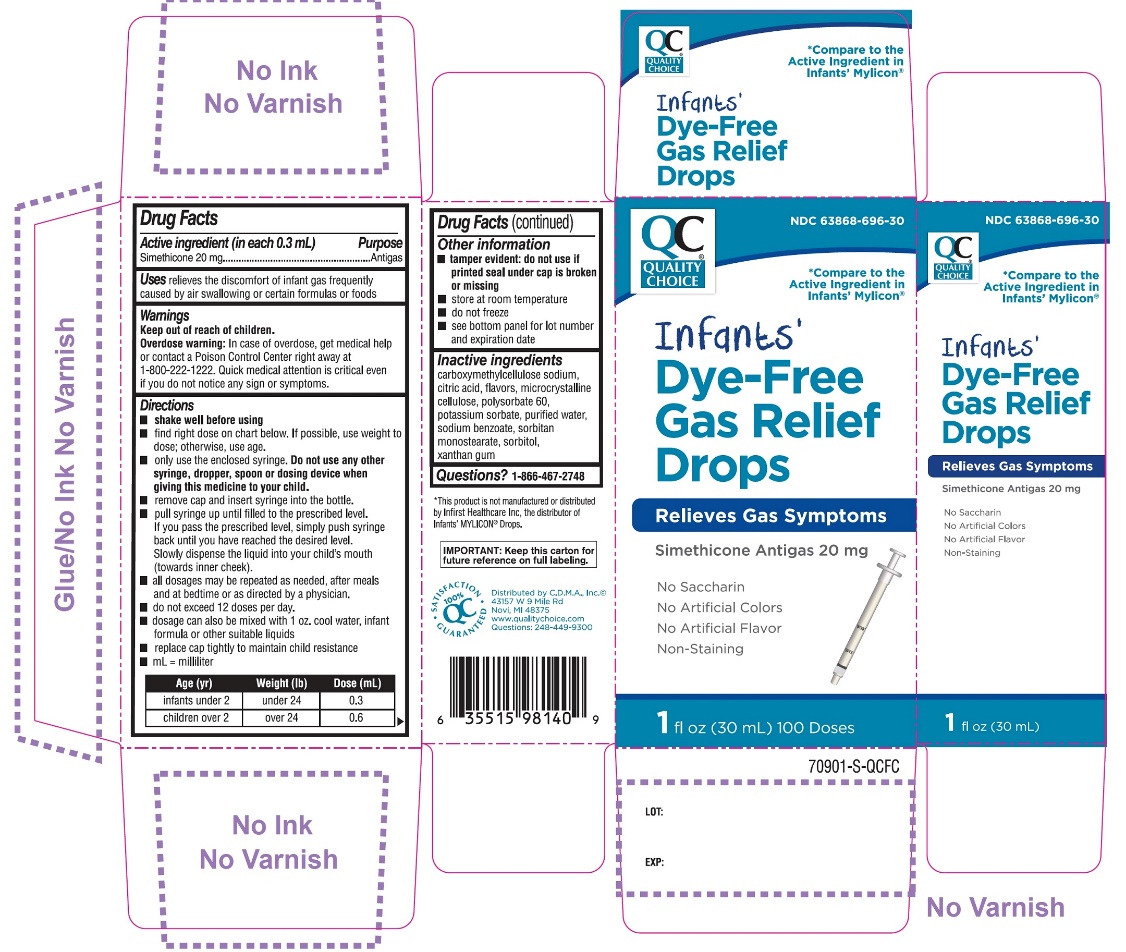 DRUG LABEL: Quality Choice Infants Dye Free Gas Relief
NDC: 63868-696 | Form: EMULSION
Manufacturer: CHAIN DRUG MARKETING ASSOCIATION
Category: otc | Type: HUMAN OTC DRUG LABEL
Date: 20251204

ACTIVE INGREDIENTS: DIMETHICONE, UNSPECIFIED 20 mg/0.3 mL
INACTIVE INGREDIENTS: CARBOXYMETHYLCELLULOSE SODIUM, UNSPECIFIED; ANHYDROUS CITRIC ACID; MICROCRYSTALLINE CELLULOSE; POLYSORBATE 60; POTASSIUM SORBATE; WATER; SODIUM BENZOATE; SORBITAN MONOSTEARATE; SORBITOL; XANTHAN GUM

Quality Choice Infants Dye Free Gas Relief Drops

Active ingredient (in each 0.3 mL)

Simethicone 20 mg

Purpose

Antigas

Uses

relieves the discomfort of infant gas frequently caused by air swallowing or certain formulas or foods

Directions

- shake well before using
- find right dose on chart below. If possible, use weight to dose; otherwise, use age.
- only use the enclosed syringe. Do not use other syringe, dropper, spoon or dosing device when giving this medicine to your child.
- remove cap and insert syringe into the bottle
- pull syringe up until filled to the prescribed level. If you pass the prescribed level, simply push syringe back until you have reached the desired level. Slowly dispense the liquid into your child’s mouth (toward inner cheek).
- all dosages may be repeated as needed, after meals and at bedtime or as directed by a physician.
- do not exceed 12 doses per day.
- dosage can also be mixed with 1 oz. cool water, infant formula or other suitable liquids
- replace cap tightly to maintain child resistance
- mL = milliliter

Age (yr) | Weight (lb) | Dose (mL)
infants under 2 | under 24 | 0.3
children over 2 | over 24 | 0.6

Other information

- tamper evident: do not use if printed seal under cap is broken or missing
- store at room temperature
- do not freeze
- see bottom panel for lot number and expiration date

Inactive ingredients

carboxymethylcellulose sodium, citric acid, flavors, microcrystalline cellulose, polysorbate 60, potassium sorbate, purified water, sodium benzoate, sorbitan monostearate, sorbitol, xanthan gum

Questions or comments ?

Call 1-866-467-2748

Principal Display Panel

NDC# 63868-696-30

QUALITY CHOICE®

*Compare to the Active Ingredient in Infants’ Mylicon®

Infants’ Dye-Free Gas Relief Drops

Relieves Gas Symptoms

Simethicone Antigas 20 mg

No Saccharin

No Artificial Colors

No Artificial Flavor

Non-Staining

1 Fl. OZ (30ml)

100 Doses

100% QC SATISFACTION GUARANTEED

Distributed by: C.D.M.A. Inc. ©

43157 W 9 Mile Rd

Novi, MI 48375

www.qualitychoice.com

Questions: 248-449-9300

*This product is not manufactured or distributed by Infirst Healthcare Inc., the distributor of Infants’ MYLICON®Drops.